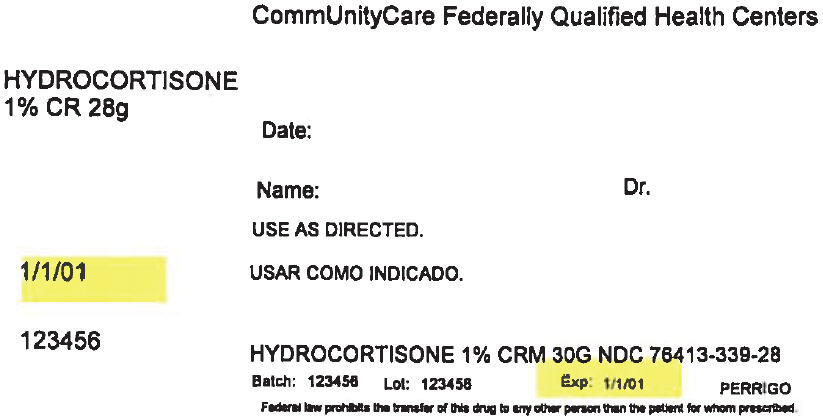 DRUG LABEL: hydrocortisone
NDC: 76413-339 | Form: CREAM
Manufacturer: Central Texas Community Health Centers
Category: otc | Type: HUMAN OTC DRUG LABEL
Date: 20170828

ACTIVE INGREDIENTS: HYDROCORTISONE 1 g/100 g
INACTIVE INGREDIENTS: ALOE VERA LEAF; POLYOXYL 20 CETOSTEARYL ETHER; CETOSTEARYL ALCOHOL; CETYL PALMITATE; GLYCERIN; ISOPROPYL MYRISTATE; METHYLPARABEN; WATER; ISOSTEARYL NEOPENTANOATE

Perrigo Hydrocortisone Cream 1% Drug Facts

Active ingredient

Hydrocortisone 1%

Purpose

Anti-itch

Uses

- temporarily relieves itching associated with minor skin irritations, inflammation, and rashes due to:
- eczema
- psoriasis
- poison ivy, oak, sumac
- insect bites
- detergents
- jewelry
- seborrheic dermatitis
- soaps
- external genital and anal itching
- other uses of this product should be only under the advice and supervision of a doctor

Warnings

For external use only

Do not use

- for the treatment of diaper rash. Ask a doctor.
- for external genital itching if you have a vaginal discharge. Ask a doctor.

When using this product

- avoid contact with the eyes
- do not begin use of any other hydrocortisone product unless you have asked a doctor
- for external anal itching do not exceed the recommended daily dosage unless directed by a doctor. In case of bleeding, consult a doctor promptly.
- do not put this product into the rectum by using fingers or any mechanical device or applicator

Stop use and ask a doctor if

- condition worsens
- symptoms persist for more than 7 days or clear up and occur again within a few days

Keep out of reach of children.

If swallowed, get medical help or contact a Poison Control Center right away.

Directions

adults and children 2 years of age and older:

- apply to affected area not more than 3 to 4 times daily

children under 2 years of age:

- do not use. Ask a doctor.

for external anal itching:

- adults: when practical, cleanse the affected area with mild soap and warm water and rinse thoroughly. Gently dry by patting or blotting with toilet tissue or a soft cloth before application of this product.
- children under 12 years of age with external anal itching: ask a doctor

Other information

- store at 20°-25°C (68°-77°F)

Inactive ingredients

aloe vera gel, ceteareth-20, cetearyl alcohol, cetyl palmitate, glycerin, isopropyl myristate, isostearyl neopentanoate, methylparaben, purified water

Questions or comments?

1-800-719-9260

PRINCIPAL DISPLAY PANEL - 28 g Tube Label

CommUnityCare Federally Qualified Health Centers

HYDROCORTISONE
1% CR 28g

Date:

Name:
Dr.

USE AS DIRECTED.

1/1/01

123456

HYDROCORTISONE 1% CRM 30G NDC 76413-339-28

Batch: 123456
Lot: 123456
Exp: 1/1/01
PERRIGO

Federal law prohibits the transfer of this drug to any other person than the patient for whom prescribed.